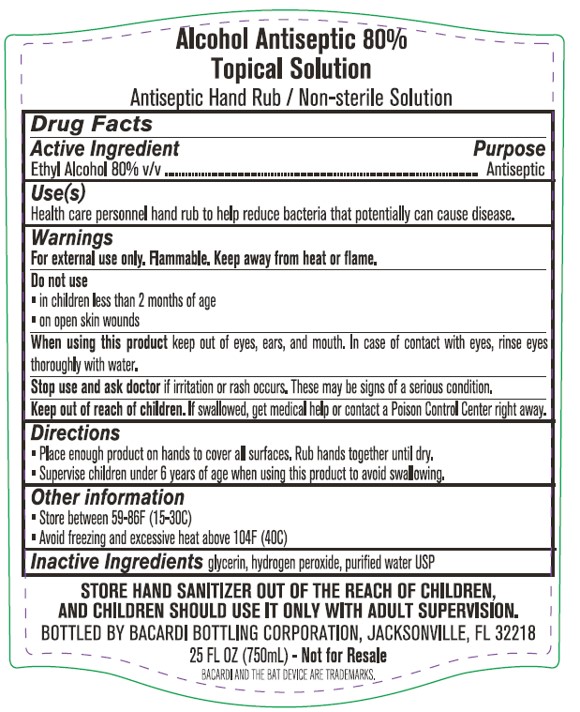 DRUG LABEL: Alcohol
NDC: 74021-0007 | Form: LIQUID
Manufacturer: Bacardi Bottling Corporation
Category: otc | Type: HUMAN OTC DRUG LABEL
Date: 20200401

ACTIVE INGREDIENTS: ALCOHOL 80 mL/100 mL
INACTIVE INGREDIENTS: GLYCERIN 1.45 mL/100 mL; HYDROGEN PEROXIDE 0.125 mL/100 mL

ACTIVE INGREDIENT

Alcohol 80% v/v

PURPOSE

Antiseptic

INDICATIONS AND USAGE

Health care personnel hand rub to help reduce bacteria that potentially can cause disease.

DO NOT USE

• in children less than 2 months of age
• on open skin wounds

. Stop use and ask a doctor if irritation or rash occurs. These may be signs of a serious condition.

Keep out of reach of children. If swallowed, get medical help or contact a Poison Control Center right away.

WARNINGS

For external use only. Flammable. Keep away from heat or flame

DOSAGE AND ADMINISTRATION

Place enough product on hands to cover all surfaces. Rub hands together until dry.

Supervise children under 6 years of age when using this product to avoid swallowing.

OTHER SAFETY INFORMATION

Store between 15-30C (59-86F)
Avoid freezing and excessive heat above 40C (104F)

INACTIVE INGREDIENT

glycerin, hydrogen peroxide, purified water USP